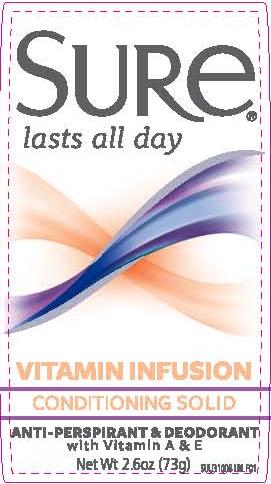 DRUG LABEL: Sure Conditioning Solid Vitamin Infusion
NDC: 41595-5441 | Form: STICK
Manufacturer: Idelle Labs, Ltd
Category: otc | Type: HUMAN OTC DRUG LABEL
Date: 20120823

ACTIVE INGREDIENTS: ALUMINUM ZIRCONIUM TRICHLOROHYDREX GLY 19 g/100 g
INACTIVE INGREDIENTS: CYCLOMETHICONE 5; STEARYL ALCOHOL; DIMETHICONE; PETROLATUM; PPG-14 BUTYL ETHER; HYDROGENATED CASTOR OIL; TALC; MINERAL OIL; DOCOSANOL

Sure Conditioning Solid Vitamin Infusion

Front Panel Display

Sure
lasts all day
Vitamin Infusion
Conditioning Solid
Anti-perspirant and Deodorant
with Vitamin A & E

Active Ingredient

Aluminum Zirconium Trichlorohydrex GLY 19% (anhydrous)

Purpose

Antiperspirant

Uses

Reduces underarm wetness

Warnings

For external use only.

Do not use on broken skin

Ask a doctor before use if you have kidney disease

Stop use

Stop use if rash or irritation occurs

Keep out of reach of children. If swallowed, get medical help or contact a Poison Control Center right away.

Directions

Apply to underarms only

Inactive Ingredients

Cyclopentasiloxane, Stearyl Alcohol, Dimethicone, Petrolatum, PPG-14 Butyl Ether, Hydrogenated Castor Oil, Talc, Fragrance, Mineral Oil, Behenyl Alcohol

Questions?

1-800-487-7273
www.suredeodorant.com
Idelle Labs, Ltd. All rights reserved.
Made in Canada and distributed by Idelle Labs, Ltd., El Paso, TX 79912
Sure® is a registered trademark of Helen of Troy Limited

label